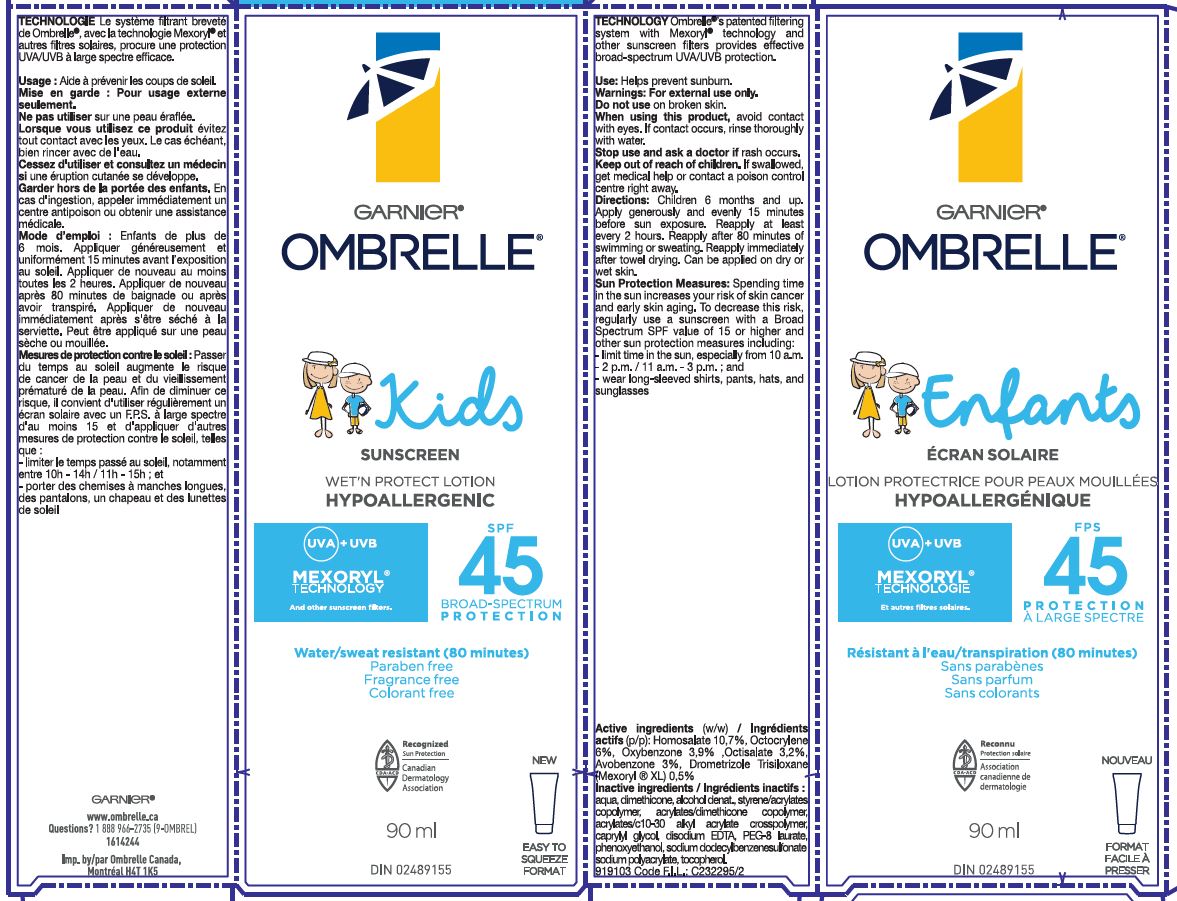 DRUG LABEL: Garnier Ombrelle Kids Wet N Protect Hypoallergenic SPF 45 Mexoryl Technology
NDC: 49967-063 | Form: LOTION
Manufacturer: L'Oreal USA Products Inc
Category: otc | Type: HUMAN OTC DRUG LABEL
Date: 20260107

ACTIVE INGREDIENTS: HOMOSALATE 107 mg/1 mL; OCTOCRYLENE 60 mg/1 mL; OXYBENZONE 39 mg/1 mL; OCTISALATE 32 mg/1 mL; AVOBENZONE 30 mg/1 mL; DROMETRIZOLE TRISILOXANE 5 mg/1 mL
INACTIVE INGREDIENTS: WATER; DIMETHICONE; ALCOHOL; CARBOMER INTERPOLYMER TYPE A (ALLYL SUCROSE CROSSLINKED); caprylyl glycol; EDETATE SODIUM; PEG-8 LAURATE; PHENOXYETHANOL; SODIUM DODECYLBENZENESULFONATE; SODIUM POLYACRYLATE (2500000 MW); TOCOPHEROL

Drug Facts

Active ingredients

Homosalate 10.7%
Octocrylene 6%
Oxybenzone 3.9%
Octisalate 3.2%
Avobenzone 3%
Drometrizole Trisiloxane 0.5%

Inactive ingredients

Aqua, Dimethicone, Alcohol Denat., Styrene/Acrylates Copolymer, Acrylates/Dimethicone Copolymer, Acrylates/C10-30 Alkyl Acrylate Crosspolymer, Caprylyl Glycol, Disodium EDTA, PEG-8 Laurate, Phenoxyethanol, Sodium Dodecylbenzenesulfonate, Sodium Polyacrylate, Tocopherol

Use:

Helps prevent sunburn.

Warnings

For external use only.

Do not use

on broken skin

When using this product,

avoid contact with eyes. If contact occurs, rinse thoroughly with water.

Stop use and ask a doctor if

rash occurs.

Keep out of reach of children.

If swallowed, get medical help or contact a Poison Control Center right away

Directions

Adults and children 6 months and up. Apply generously and evenly 15 minutes before sun exposure. Reapply at least every 2 hours, after 80 minutes of swimming or sweating and immediately after towel drying. Can be applied on dry or wet skin.